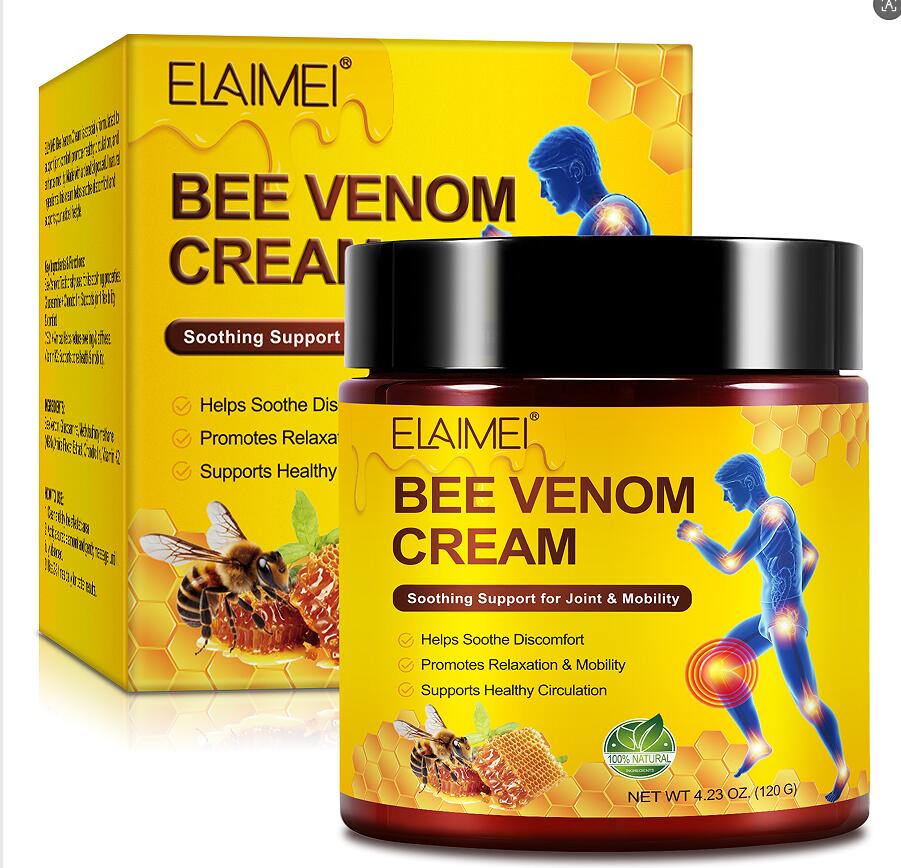 DRUG LABEL: ELAIMEI Bee Venom Cream
NDC: 83804-013 | Form: CREAM
Manufacturer: Shenzhen Shandian Jingling Technology Co., Ltd.
Category: otc | Type: HUMAN OTC DRUG LABEL
Date: 20260127

ACTIVE INGREDIENTS: APIS MELLIFERA VENOM 55 g/100 g
INACTIVE INGREDIENTS: GLUCOSAMINE; DIMETHYL SULFONE; CHONDROITIN SULFATE (PORCINE); ARNICA MONTANA FLOWER; MENAQUINONE 6

83804-013 ELAIMEI Bee Venom Cream

ACTIVE INGREDIENT

Bee Venom

PURPOSE

Relieve discomfort

INDICATIONS AND USAGE

ELAlMEl Bee Venom Cream is specially formulated tosupport joint comfort, promote healthy circulation, andenhance mobility. Made with a blend of powerful natura!ingredients, this cream helps soothe discomfort andsupports your active lifestyle.

WARNINGS

For external use only.

Do not apply to broken or irritated skin.
Do not use if you areallergic to Bee Venom or any of the listed ingredientsIf irritation occurs, discontinue use and consult a

Do not use if you areallergic to Bee Venom or any of the listed ingredientsIf irritation occurs, discontinue use and consult a

WHEN USING

For external use only. Avoid contact with eyes.

Keep out of reach of children

DOSAGE AND ADMINISTRATION

1. Clean and dry the affected area.
2. Apply a suitable amount and gently massage untilfully absorbed.
3. Use 2-3 times daily for better results.

INACTIVE INGREDIENT

Glucosamine
Methylsulfonylmethane (MSM)
Arnica Flower Extract
Chondroitin
Vitamin K2